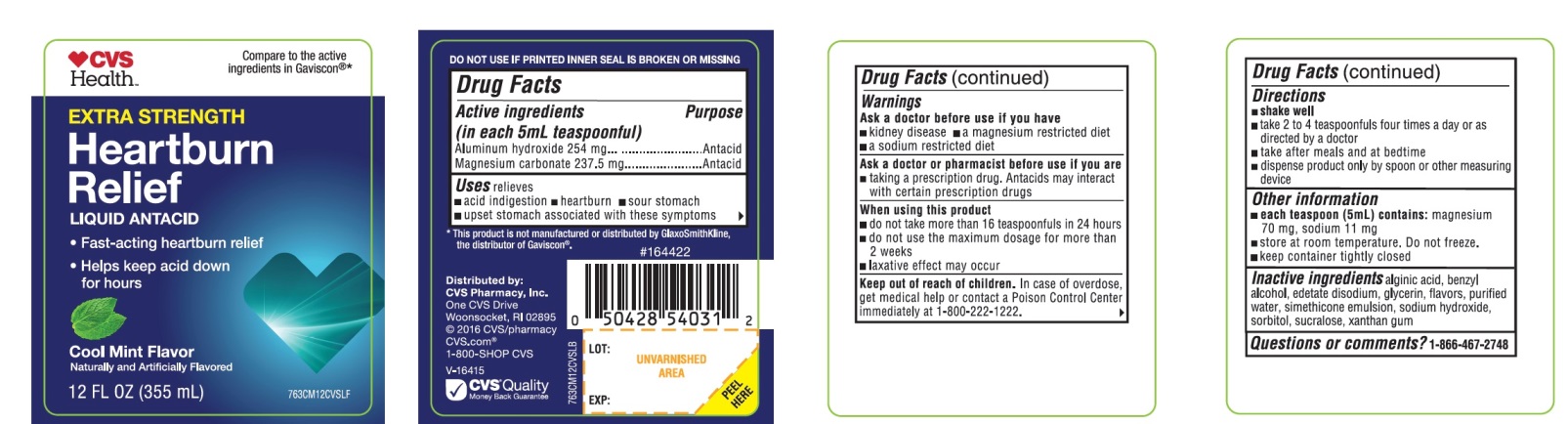 DRUG LABEL: CVS Health Extra Strength

NDC: 69842-376 | Form: LIQUID
Manufacturer: CVS PHARMACY
Category: otc | Type: HUMAN OTC DRUG LABEL
Date: 20251210

ACTIVE INGREDIENTS: ALUMINUM HYDROXIDE 254 mg/5 mL; MAGNESIUM CARBONATE 237.5 mg/5 mL
INACTIVE INGREDIENTS: ALGINIC ACID; BENZYL ALCOHOL; EDETATE DISODIUM; GLYCERIN; WATER; DIMETHICONE, UNSPECIFIED; SODIUM HYDROXIDE; SORBITOL; SUCRALOSE; XANTHAN GUM

CVS Health Liquid Antacid Extra Strength Cool Mint Flavor 355mL

Active ingredients (in each 5mL teaspoonful)

Aluminum hydroxide 254mg

Magnesium carbonate 237.5mg

Purpose

Antacid

Antacid

Uses

relieves

- acid indigestion
- heartburn
- sour stomach
- upset stomach associated with these symptoms

Warnings

Ask a doctor or pharmacist before use if you are

- taking a prescription drug. Antacids may interact with certain prescription drugs.
- if you are on a sodium-restricted diet

When using this product

- do not take more than 16 teaspoonful in 24 hours
- do not use the maximum dosage for more than 2 weeks
- laxative effect may occur

Keep out of reach of children.

In case of overdose, get medical help or contact a Poison Control Center immediately at 1-800-222-1222.

Directions

- shake well
- take 2-4 teaspoonful four times a day or as directed by a doctor
- take after meals and at bedtime
- dispense product only by spoon or other measuring device

Other information

- each teaspoon (5mL) contains:magnesium 80mg, sodium 14mg
- store at room temperature. Do not freeze.
- keep container tightly closed

Inactive Ingredients

alginic acid, benzyl alcohol, edetate disodium, flavors, glycerin, purified water, simethicone emulsion, sodium hydroxide, sorbitol, sucralose, xanthan gum

Questions or comments?

1-866-467-2748

DO NOT USE IF PRINTED INNER SEAL IS BROKEN OR MISSING

Principal Display Panel

CVS Health™

Compare to the active ingredients Gaviscon®*

NDC# 69842-376-12

EXTRA STRENGTH

Heartburn Relief

LIQUID ANTACID

- Fast-Acting Heartburn Relief
- Helps Keep Acid Down for Hours

Cool Mint Flavor

Naturally and Artificially Flavored

12FL OZ (355ml)

*This product is not manufactured or distributed by GlaxoSmithKline, the distributor of Gaviscon®.

Distributed by:

CVS Pharmacy, Inc.
One CVS Drive

Woonsocket, RI 02895

2016 CVS/pharmacy

CVS.com, 1-800-SHOP CVS

V-16415

CVS®Quality

Money Back Guarantee